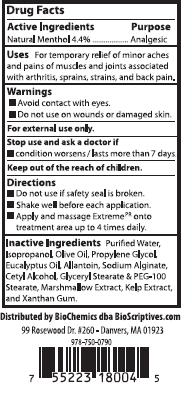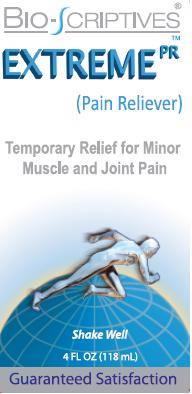 DRUG LABEL: Bio-Scriptives Extreme PR
NDC: 60608-015 | Form: LOTION
Manufacturer: BioChemics, Inc.
Category: otc | Type: HUMAN OTC DRUG LABEL
Date: 20110722

ACTIVE INGREDIENTS: Menthol 5.11 g/113 g
INACTIVE INGREDIENTS: WATER; ISOPROPYL ALCOHOL; OLIVE OIL; PROPYLENE GLYCOL; EUCALYPTUS OIL; SODIUM ALGINATE; CETYL ALCOHOL; GLYCERYL MONOSTEARATE; POLYOXYL 100 STEARATE; SEAWEED; ALTHAEA OFFICINALIS LEAF; ALLANTOIN; XANTHAN GUM

Drug Facts

Active Ingredient

Natural Menthol 4.4%

Purpose

Analgesic

Uses

For temporary relief of minor aches and pains of muscles and joints associated with arthritis, sprains, strains, and back pain.

Warnings

■ Avoid Contact with eyes.
■ Do not use on wounds or damaged skin.
For external use only.

Stop use and ask doctor if

■ condition worsens/lasts more than 7 days.

Keep out of the reach of children.

Directions

■ Do not use if safety seal is broken.
■ Shake well before each application.
■ Apply and massage Extreme PR™ onto treatment area up to 4 times daily.

Inactive Ingredients

Deionized Water, Isopropanol, Olive Oil, Propylene Glycol, Eucalyptus Oil, Sodium Alginate, Cetyl Alcohol, Glyceryl Stearate and PEG-100 Stearate, Kelp Extract, Marshmallow Extract, Allantoin, and Xanthan Gum.

Questions:

Distributed by BioChemics

dba Bio-Scriptives (978) 750-0790

99 Rosewood Drive, #260

Danvers, MA 01923